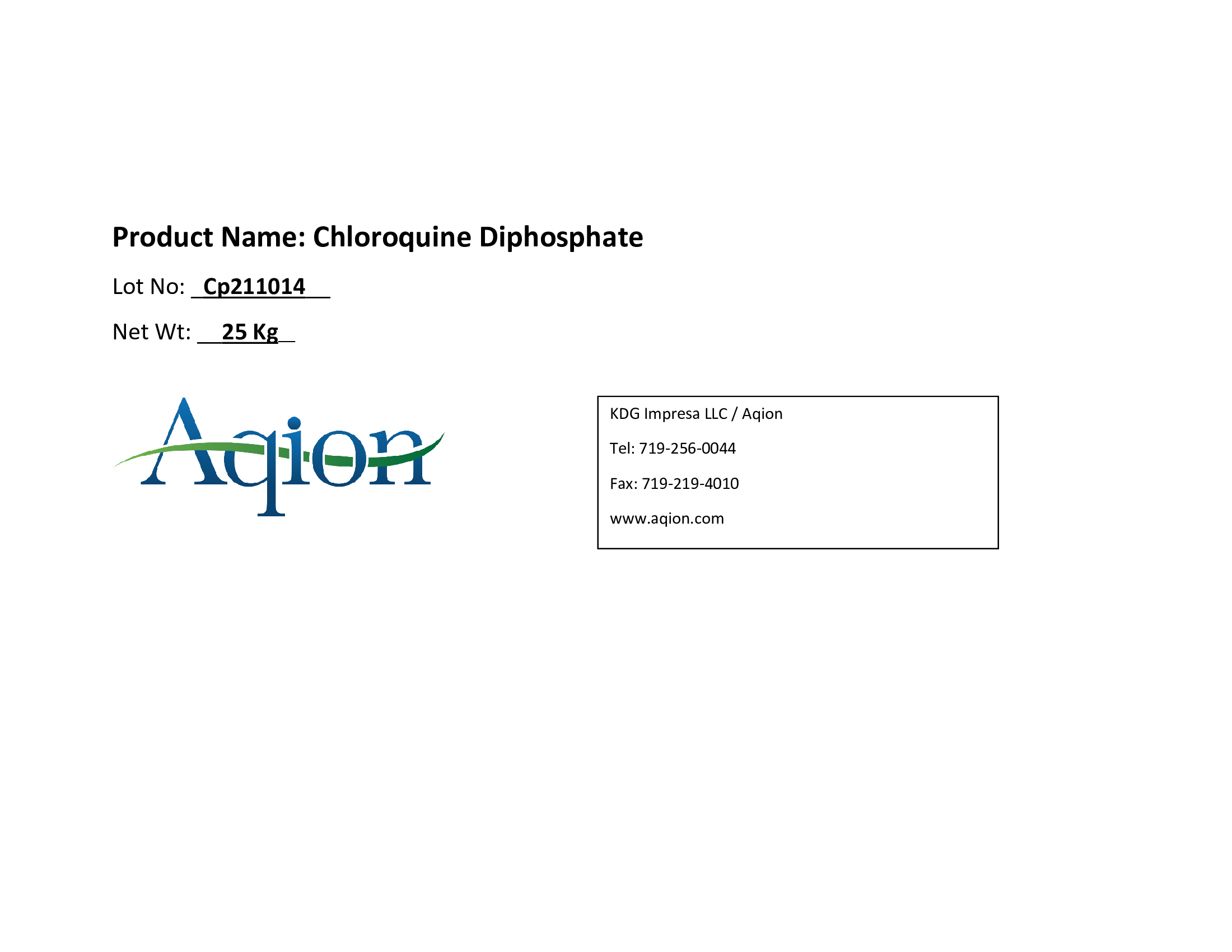 DRUG LABEL: Chloroquine Diphosphate
NDC: 43457-540 | Form: POWDER
Manufacturer: KDG Impresa LLC, Aqion
Category: other | Type: BULK INGREDIENT - ANIMAL DRUG
Date: 20220223

ACTIVE INGREDIENTS: CHLOROQUINE DIPHOSPHATE, (R)- 1 kg/1 kg

Chloroquine Diphosphate